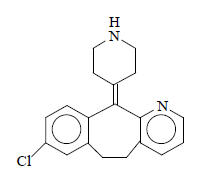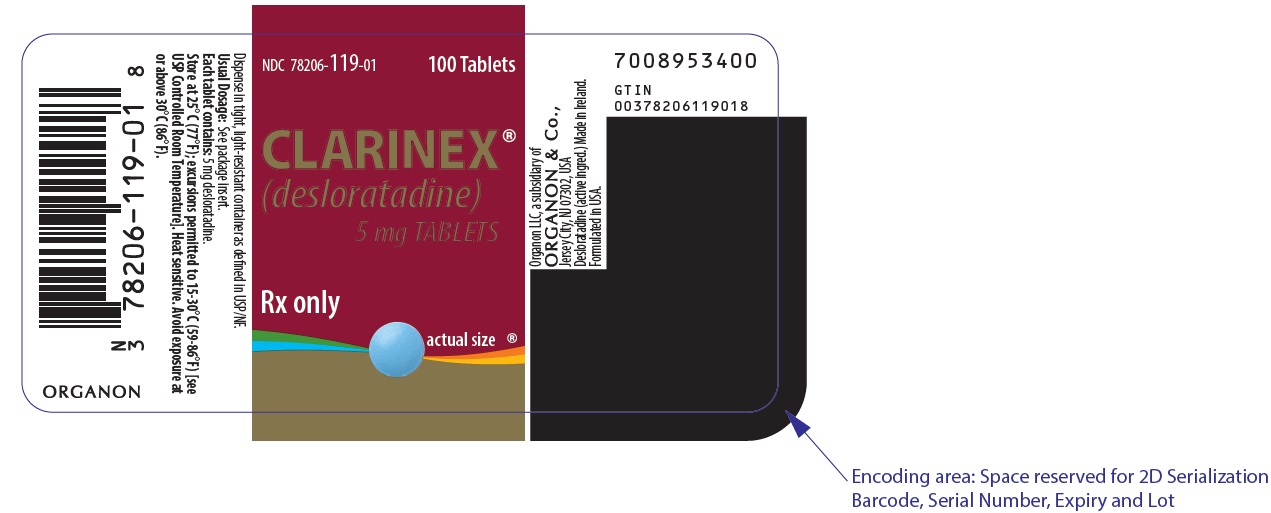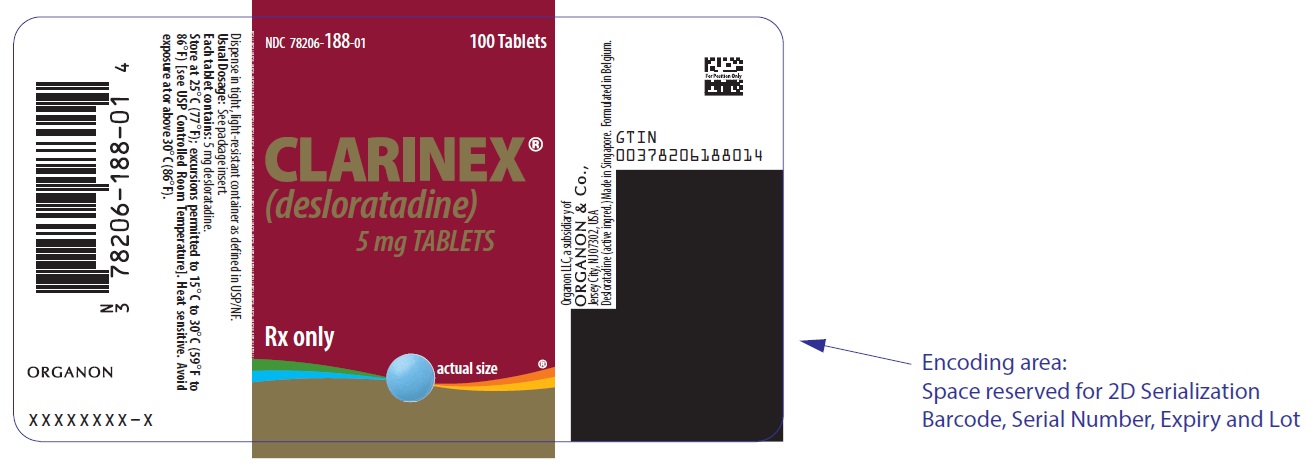 DRUG LABEL: Clarinex
NDC: 78206-119 | Form: TABLET, FILM COATED
Manufacturer: Organon LLC
Category: prescription | Type: HUMAN PRESCRIPTION DRUG LABEL
Date: 20250517

ACTIVE INGREDIENTS: DESLORATADINE 5 mg/1 1
INACTIVE INGREDIENTS: DIBASIC CALCIUM PHOSPHATE DIHYDRATE; MICROCRYSTALLINE CELLULOSE; STARCH, CORN; TALC; CARNAUBA WAX; WHITE WAX; LACTOSE MONOHYDRATE; HYPROMELLOSE, UNSPECIFIED; TITANIUM DIOXIDE; POLYETHYLENE GLYCOL, UNSPECIFIED; FD&C Blue No. 2; ALUMINUM OXIDE

HIGHLIGHTS OF PRESCRIBING INFORMATION

These highlights do not include all the information needed to use CLARINEX safely and effectively. See full prescribing information for CLARINEX.
CLARINEX® (desloratadine) Tablets, RediTabs®, and Oral Solution for oral use
Initial U.S. Approval: 2001

1 INDICATIONS AND USAGE

CLARINEX is a histamine-1 (H1) receptor antagonist indicated for:

- Seasonal Allergic Rhinitis: relief of nasal and non-nasal symptoms in patients 2 years of age and older. (1.1)
- Perennial Allergic Rhinitis: relief of nasal and non-nasal symptoms in patients 6 months of age and older. (1.2)
- Chronic Idiopathic Urticaria: symptomatic relief of pruritus, reduction in the number of hives, and size of hives in patients 6 months of age and older. (1.3)

2 DOSAGE AND ADMINISTRATION

Dosage (by age):

Adults and Adolescents 12 Years of Age and Over:

- CLARINEX Tablets - one 5 mg tablet once daily or
- CLARINEX RediTabs Tablets - one 5 mg tablet once daily or
- CLARINEX Oral Solution - 2 teaspoonfuls (5 mg in 10 mL) once daily (2)

Children 6 to 11 Years of Age:

- CLARINEX Oral Solution - 1 teaspoonful (2.5 mg in 5 mL) once daily or
- CLARINEX RediTabs Tablets - one 2.5 mg tablet once daily (2)

Children 12 Months to 5 Years of Age:

- CLARINEX Oral Solution - ½ teaspoonful (1.25 mg in 2.5 mL) once daily (2)

Children 6 to 11 Months of Age:

- CLARINEX Oral Solution - 2 mL (1 mg) once daily (2)

3 DOSAGE FORMS AND STRENGTHS

- CLARINEX Tablets - 5 mg (3)

4 CONTRAINDICATIONS

- Hypersensitivity (4, 6.2)

5 WARNINGS AND PRECAUTIONS

- Hypersensitivity reactions including rash, pruritus, urticaria, edema, dyspnea, and anaphylaxis have been reported. In such cases, stop CLARINEX at once and consider alternative treatments. (5.1)

6 ADVERSE REACTIONS

- The most common adverse reactions (reported in ≥2% of adult and adolescent patients with allergic rhinitis and greater than placebo) were pharyngitis, dry mouth, myalgia, fatigue, somnolence, dysmenorrhea. (6.1)

To report SUSPECTED ADVERSE REACTIONS, contact Organon LLC, a subsidiary of Organon & Co., at 1-844-674-3200 or FDA at 1-800-FDA-1088 or www.fda.gov/medwatch.

8 USE IN SPECIFIC POPULATIONS

- Renal impairment: dosage adjustment is recommended (2.5, 8.6, 12.3)
- Hepatic impairment: dosage adjustment is recommended (2.5, 8.7, 12.3)

FULL PRESCRIBING INFORMATION

1 INDICATIONS AND USAGE

1.1 Seasonal Allergic Rhinitis

CLARINEX® is indicated for the relief of the nasal and non-nasal symptoms of seasonal allergic rhinitis in patients 2 years of age and older.

1.2 Perennial Allergic Rhinitis

CLARINEX is indicated for the relief of the nasal and non-nasal symptoms of perennial allergic rhinitis in patients 6 months of age and older.

1.3 Chronic Idiopathic Urticaria

CLARINEX is indicated for the symptomatic relief of pruritus, reduction in the number of hives, and size of hives, in patients with chronic idiopathic urticaria 6 months of age and older.

2 DOSAGE AND ADMINISTRATION

Although the oral solution and the orally disintegrating tablet formulation of desloratadine may be available in the marketplace, CLARINEX® Oral Solution and CLARINEX® RediTabs® Tablets are no longer marketed.

CLARINEX Tablets, Oral Solution, or RediTabs Tablets may be taken without regard to meals. Place CLARINEX (desloratadine) RediTabs Tablets on the tongue and allow to disintegrate before swallowing. Tablet disintegration occurs rapidly. Administer with or without water. Take tablet immediately after opening the blister.

The age-appropriate dose of CLARINEX Oral Solution should be administered with a commercially available measuring dropper or syringe that is calibrated to deliver 2 mL and 2.5 mL (½ teaspoon).

2.1 Adults and Adolescents 12 Years of Age and Over

The recommended dose of CLARINEX Tablets or CLARINEX RediTabs Tablets is one 5-mg tablet once daily. The recommended dose of CLARINEX Oral Solution is 2 teaspoonfuls (5 mg in 10 mL) once daily.

2.2 Children 6 to 11 Years of Age

The recommended dose of CLARINEX Oral Solution is 1 teaspoonful (2.5 mg in 5 mL) once daily. The recommended dose of CLARINEX RediTabs Tablets is one 2.5-mg tablet once daily.

2.3 Children 12 Months to 5 Years of Age

The recommended dose of CLARINEX Oral Solution is ½ teaspoonful (1.25 mg in 2.5 mL) once daily.

2.4 Children 6 to 11 Months of Age

The recommended dose of CLARINEX Oral Solution is 2 mL (1 mg) once daily.

2.5 Adults with Hepatic or Renal Impairment

In adult patients with liver or renal impairment, a starting dose of one 5-mg tablet every other day is recommended based on pharmacokinetic data. Dosing recommendation for children with liver or renal impairment cannot be made due to lack of data [see Clinical Pharmacology (12.3)].

3 DOSAGE FORMS AND STRENGTHS

CLARINEX Tablets are supplied as:

- Light blue, film-coated tablets embossed with “C5” containing 5 mg desloratadine.
- Light blue, film-coated tablets embossed with an elongated letters “S” and “P” on one side and plain on the other, containing 5 mg desloratadine.

4 CONTRAINDICATIONS

CLARINEX Tablets, RediTabs, and Oral Solution are contraindicated in patients who are hypersensitive to this medication or to any of its ingredients or to loratadine [see Warnings and Precautions (5.1) and Adverse Reactions (6.2)].

5 WARNINGS AND PRECAUTIONS

5.1 Hypersensitivity Reactions

Hypersensitivity reactions including rash, pruritus, urticaria, edema, dyspnea, and anaphylaxis have been reported after administration of desloratadine. If such a reaction occurs, therapy with CLARINEX should be stopped and alternative treatment should be considered. [See Adverse Reactions (6.2).]

6 ADVERSE REACTIONS

The following adverse reactions are discussed in greater detail in other sections of the label:

- Hypersensitivity reactions. [See Warnings and Precautions (5.1).]

6.1 Clinical Trials Experience

Because clinical trials are conducted under widely varying conditions, adverse reaction rates observed in the clinical trials of a drug cannot be directly compared to rates in the clinical trials of another drug and may not reflect the rates observed in clinical practice.

Adults and Adolescents

Allergic Rhinitis: In multiple-dose placebo-controlled trials, 2834 patients ages 12 years or older received CLARINEX Tablets at doses of 2.5 mg to 20 mg daily, of whom 1655 patients received the recommended daily dose of 5 mg. In patients receiving 5 mg daily, the rate of adverse events was similar between CLARINEX and placebo-treated patients. The percent of patients who withdrew prematurely due to adverse events was 2.4% in the CLARINEX group and 2.6% in the placebo group. There were no serious adverse events in these trials in patients receiving desloratadine. All adverse events that were reported by greater than or equal to 2% of patients who received the recommended daily dose of CLARINEX Tablets (5 mg once daily), and that were more common with CLARINEX Tablets than placebo, are listed in Table 1.

Table 1: Incidence of Adverse Events Reported by ≥2% of Adult and Adolescent Allergic Rhinitis Patients Receiving CLARINEX Tablets
Adverse Event | CLARINEX Tablets 5 mg (n=1655) | Placebo (n=1652)
Infections and Infestations
Pharyngitis | 4.1% | 2.0%
Nervous System Disorders
Somnolence | 2.1% | 1.8%
Gastrointestinal Disorders
Dry Mouth | 3.0% | 1.9%
Musculoskeletal and Connective Tissue Disorders
Myalgia | 2.1% | 1.8%
Reproductive System and Breast Disorders
Dysmenorrhea | 2.1% | 1.6%
General Disorders and Administration Site Conditions
Fatigue | 2.1% | 1.2%

The frequency and magnitude of laboratory and electrocardiographic abnormalities were similar in CLARINEX and placebo-treated patients.

There were no differences in adverse events for subgroups of patients as defined by gender, age, or race.

Chronic Idiopathic Urticaria: In multiple-dose, placebo-controlled trials of chronic idiopathic urticaria, 211 patients ages 12 years or older received CLARINEX Tablets and 205 received placebo. Adverse events that were reported by greater than or equal to 2% of patients who received CLARINEX Tablets and that were more common with CLARINEX than placebo were (rates for CLARINEX and placebo, respectively): headache (14%, 13%), nausea (5%, 2%), fatigue (5%, 1%), dizziness (4%, 3%), pharyngitis (3%, 2%), dyspepsia (3%, 1%), and myalgia (3%, 1%).

Pediatrics

Two hundred and forty-six pediatric subjects 6 months to 11 years of age received CLARINEX Oral Solution for 15 days in three placebo-controlled clinical trials. Pediatric subjects aged 6 to 11 years received 2.5 mg once a day, subjects aged 1 to 5 years received 1.25 mg once a day, and subjects 6 to 11 months of age received 1.0 mg once a day.

In subjects 6 to 11 years of age, no individual adverse event was reported by 2 percent or more of the subjects.

In subjects 2 to 5 years of age, adverse events reported for CLARINEX and placebo in at least 2 percent of subjects receiving CLARINEX Oral Solution and at a frequency greater than placebo were fever (5.5%, 5.4%), urinary tract infection (3.6%, 0%) and varicella (3.6%, 0%).

In subjects 12 months to 23 months of age, adverse events reported for the CLARINEX product and placebo in at least 2 percent of subjects receiving CLARINEX Oral Solution and at a frequency greater than placebo were fever (16.9%, 12.9%), diarrhea (15.4%, 11.3%), upper respiratory tract infections (10.8%, 9.7%), coughing (10.8%, 6.5%), appetite increased (3.1%, 1.6%), emotional lability (3.1%, 0%), epistaxis (3.1%, 0%), parasitic infection (3.1%, 0%), pharyngitis (3.1%, 0%), rash maculopapular (3.1%, 0%).

In subjects 6 months to 11 months of age, adverse events reported for CLARINEX and placebo in at least 2 percent of subjects receiving CLARINEX Oral Solution and at a frequency greater than placebo were upper respiratory tract infections (21.2%, 12.9%), diarrhea (19.7%, 8.1%), fever (12.1%, 1.6%), irritability (12.1%, 11.3%), coughing (10.6%, 9.7%), somnolence (9.1%, 8.1%), bronchitis (6.1%, 0%), otitis media (6.1%, 1.6%), vomiting (6.1%, 3.2%), anorexia (4.5%, 1.6%), pharyngitis (4.5%, 1.6%), insomnia (4.5%, 0%), rhinorrhea (4.5%, 3.2%), erythema (3.0%, 1.6%), and nausea (3.0%, 0%).

There were no clinically meaningful changes in any electrocardiographic parameter, including the QTc interval. Only one of the 246 pediatric subjects receiving CLARINEX Oral Solution in the clinical trials discontinued treatment because of an adverse event.

6.2 Post-Marketing Experience

Because adverse events are reported voluntarily from a population of uncertain size, it is not always possible to reliably estimate their frequency or establish a causal relationship to drug exposure. The following spontaneous adverse events have been reported during the marketing of desloratadine:

Cardiac disorders: tachycardia, palpitations

Respiratory, thoracic and mediastinal disorders: dyspnea

Skin and subcutaneous tissue disorders: rash, pruritus

Nervous system disorders: psychomotor hyperactivity, movement disorders (including dystonia, tics, and extrapyramidal symptoms), seizures (reported in patients with and without a known seizure disorder)

Immune system disorders: hypersensitivity reactions (such as urticaria, edema and anaphylaxis)

Investigations: elevated liver enzymes including bilirubin

Hepatobiliary disorders: hepatitis

Metabolism and nutrition disorders: increased appetite

7 DRUG INTERACTIONS

7.1 Inhibitors of Cytochrome P450 3A4

In controlled clinical studies co-administration of desloratadine with ketoconazole, erythromycin, or azithromycin resulted in increased plasma concentrations of desloratadine and 3 hydroxydesloratadine, but there were no clinically relevant changes in the safety profile of desloratadine. [See Clinical Pharmacology (12.3).]

7.2 Fluoxetine

In controlled clinical studies co-administration of desloratadine with fluoxetine, a selective serotonin reuptake inhibitor (SSRI), resulted in increased plasma concentrations of desloratadine and 3 hydroxydesloratadine, but there were no clinically relevant changes in the safety profile of desloratadine. [See Clinical Pharmacology (12.3).]

7.3 Cimetidine

In controlled clinical studies co-administration of desloratadine with cimetidine, a histamine H2-receptor antagonist, resulted in increased plasma concentrations of desloratadine and 3 hydroxydesloratadine, but there were no clinically relevant changes in the safety profile of desloratadine. [See Clinical Pharmacology (12.3).]

8 USE IN SPECIFIC POPULATIONS

8.1 Pregnancy

Risk Summary

The limited available data with CLARINEX in pregnant women are not sufficient to inform a drug-associated risk for major birth defects and miscarriage. There are no adequate and well-controlled studies in pregnant women. Desloratadine given during organogenesis to pregnant rats was not teratogenic at the summed area under the concentration-time curve (AUC)-based exposures of desloratadine and its metabolite approximately 320 times that at the recommended human daily oral dose (RHD) of 5 mg/day. Desloratadine given during organogenesis to pregnant rabbits was not teratogenic at the AUC-based exposures of desloratadine approximately 230 times that at the RHD. Desloratadine given to pregnant rats during organogenesis through lactation resulted in reduced body weight and slow righting reflex of F1 pups at the summed AUC-based exposures of desloratadine and its metabolite approximately 70 times or greater than that at the RHD [see Data].

The estimated background risk of major birth defects and miscarriage for the indicated populations is unknown. In the U.S. general population, the estimated background risk of major birth defects and miscarriage in clinically recognized pregnancies is 2-4% and 15-20%, respectively.

Data

Animal Data

Desloratadine was given orally during organogenesis to pregnant rats at doses of 6, 24 and 48 mg/kg/day (approximately 50, 200 and 320 times the summed AUC-based exposure of desloratadine and its metabolite at the RHD). No fetal malformations were present. Reduced fetal weights and skeletal variations noted at doses of 24 and 48 mg/kg/day were likely secondary to the maternal toxicities of reduced body weight gain and food consumption observed at the same doses. Desloratadine was also given orally during organogenesis to pregnant rabbits at doses of 15, 30 and 60 mg/kg/day (approximately 30, 70 and 230 times the AUC-based exposure of desloratadine at the RHD). No adverse effects to the fetus were noted. Reduced maternal body weight gain was noted in rabbits at 60 mg/kg/day. In a peri- and post-natal development study, desloratadine was given to rats orally during the peri-natal (Gestation Day 6) through lactation periods (Postpartum Day 21) at doses of 3, 9 and 18 mg/kg/day. Reduced body weight and slow righting reflex were reported in F1 pups at doses of 9 mg/kg/day or greater (approximately 70 times or greater than the summed AUC-based exposure of desloratadine and its metabolite at the RHD). Desloratadine had no effect on F1 pup development at 3 mg/kg/day (approximately 10 times the summed AUC-based exposure of desloratadine and its metabolite at the RHD). Maternal toxicities including reduced body weight gain and food consumption were noted at 18 mg/kg/day for F0 dams. F1 offspring were subsequently mated and there was no developmental toxicity for F2 pups observed.

8.2 Lactation

Risk Summary

Desloratadine passes into breast milk. There are not sufficient data on the effects of desloratadine on the breastfed infant or the effects of desloratadine on milk production. The decision should be made whether to discontinue nursing or to discontinue desloratadine, taking into account the developmental and health benefits of breastfeeding, the nursing mother's clinical need, and any potential adverse effects on the breastfed infant from desloratadine or from the underlying maternal condition.

8.3 Females and Males of Reproductive Potential

Infertility

There are no data available on human infertility associated with desloratadine.

There were no clinically relevant effects of desloratadine on female fertility in rats. A male specific decrease in fertility occurred at an oral desloratadine dose of 12 mg/kg or greater in rats (approximately 65 times the summed AUC-based exposure of desloratadine and its metabolite at the RHD). Male fertility was unaffected at a desloratadine dose of 3 mg/kg (approximately 10 times the summed AUC-based exposure of desloratadine and its metabolite at the RHD). [See Nonclinical Toxicology (13.1).]

8.4 Pediatric Use

The recommended dose of CLARINEX Oral Solution in the pediatric population is based on cross-study comparison of the plasma concentration of CLARINEX in adults and pediatric subjects. The safety of CLARINEX Oral Solution has been established in 246 pediatric subjects aged 6 months to 11 years in three placebo-controlled clinical studies. Since the course of seasonal and perennial allergic rhinitis and chronic idiopathic urticaria and the effects of CLARINEX are sufficiently similar in the pediatric and adult populations, it allows extrapolation from the adult efficacy data to pediatric patients. The effectiveness of CLARINEX Oral Solution in these age groups is supported by evidence from adequate and well-controlled studies of CLARINEX Tablets in adults. The safety and effectiveness of CLARINEX Tablets or CLARINEX Oral Solution have not been demonstrated in pediatric patients less than 6 months of age. [See Clinical Pharmacology (12.3).]

The CLARINEX RediTabs 2.5-mg tablet has not been evaluated in pediatric patients. Bioequivalence of the CLARINEX RediTabs Tablet and the previously marketed RediTabs Tablet was established in adults. In conjunction with the dose-finding studies in pediatrics described, the pharmacokinetic data for CLARINEX RediTabs supports the use of the 2.5-mg dose strength in pediatric patients 6 to 11 years of age.

8.5 Geriatric Use

Clinical studies of desloratadine did not include sufficient numbers of subjects aged 65 and over to determine whether they respond differently from younger subjects. Other reported clinical experience has not identified differences between the elderly and younger patients. In general, dose selection for an elderly patient should be cautious, reflecting the greater frequency of decreased hepatic, renal, or cardiac function, and of concomitant disease or other drug therapy. [See Clinical Pharmacology (12.3).]

8.6 Renal Impairment

Dosage adjustment for patients with renal impairment is recommended [see Dosage and Administration (2.5) and Clinical Pharmacology (12.3)].

8.7 Hepatic Impairment

Dosage adjustment for patients with hepatic impairment is recommended [see Dosage and Administration (2.5) and Clinical Pharmacology (12.3)].

9 DRUG ABUSE AND DEPENDENCE

There is no information to indicate that abuse or dependency occurs with CLARINEX Tablets.

10 OVERDOSAGE

In the event of overdose, consider standard measures to remove any unabsorbed drug. Symptomatic and supportive treatment is recommended. Desloratadine and 3-hydroxydesloratadine are not eliminated by hemodialysis.

Information regarding acute overdosage is limited to experience from post-marketing adverse event reports and from clinical trials conducted during the development of the CLARINEX product. In a dose-ranging trial, at doses of 10 mg and 20 mg/day somnolence was reported.

In another study, no clinically relevant adverse events were reported in normal male and female volunteers who were given single daily doses of CLARINEX 45 mg for 10 days [see Clinical Pharmacology (12.2)].

11 DESCRIPTION

CLARINEX (desloratadine) Tablets are light blue, round, film-coated tablets containing 5 mg desloratadine, an antihistamine, to be administered orally. CLARINEX Tablets also contain the following excipients: dibasic calcium phosphate dihydrate USP, microcrystalline cellulose NF, corn starch NF, talc USP, carnauba wax NF, white wax NF, coating material consisting of lactose monohydrate, hypromellose, titanium dioxide, polyethylene glycol, and FD&C Blue #2 Aluminum Lake.

Desloratadine is a white to off-white powder that is slightly soluble in water, but very soluble in ethanol and propylene glycol. It has an empirical formula: C19H19ClN2 and a molecular weight of 310.8. The chemical name is 8-chloro-6,11-dihydro-11-(4-piperdinylidene)-5H-benzo[5,6]cyclohepta[1,2-b]pyridine and has the following structure:

12 CLINICAL PHARMACOLOGY

12.1 Mechanism of Action

Desloratadine is a long-acting tricyclic histamine antagonist with selective H1-receptor histamine antagonist activity. Receptor binding data indicates that at a concentration of 2–3 ng/mL (7 nanomolar), desloratadine shows significant interaction with the human histamine H1-receptor. Desloratadine inhibited histamine release from human mast cells in vitro. Results of a radiolabeled tissue distribution study in rats and a radioligand H1-receptor binding study in guinea pigs showed that desloratadine did not readily cross the blood brain barrier. The clinical significance of this finding is unknown.

12.2 Pharmacodynamics

Wheal and Flare: Human histamine skin wheal studies following single and repeated 5-mg doses of desloratadine have shown that the drug exhibits an antihistaminic effect by 1 hour; this activity may persist for as long as 24 hours. There was no evidence of histamine-induced skin wheal tachyphylaxis within the desloratadine 5-mg group over the 28-day treatment period. The clinical relevance of histamine wheal skin testing is unknown.

Effects on QTc: Single daily doses of 45 mg were given to normal male and female volunteers for 10 days. All ECGs obtained in this study were manually read in a blinded fashion by a cardiologist. In CLARINEX-treated subjects, there was an increase in mean heart rate of 9.2 bpm relative to placebo. The QT interval was corrected for heart rate (QTc) by both the Bazett and Fridericia methods. Using the QTc (Bazett) there was a mean increase of 8.1 msec in CLARINEX-treated subjects relative to placebo. Using QTc (Fridericia) there was a mean increase of 0.4 msec in CLARINEX-treated subjects relative to placebo. No clinically relevant adverse events were reported.

12.3 Pharmacokinetics

Absorption

Following oral administration of a desloratadine 5-mg tablet once daily for 10 days to normal healthy volunteers, the mean time to maximum plasma concentrations (Tmax) occurred at approximately 3 hours post dose and mean steady state peak plasma concentrations (Cmax) and AUC of 4 ng/mL and 56.9 ng∙hr/mL were observed, respectively. Neither food nor grapefruit juice had an effect on the bioavailability (Cmax and AUC) of desloratadine.

The pharmacokinetic profile of CLARINEX Oral Solution was evaluated in a three-way crossover study in 30 adult volunteers. A single dose of 10 mL of CLARINEX Oral Solution containing 5 mg of desloratadine was bioequivalent to a single dose of 5-mg CLARINEX Tablet. Food had no effect on the bioavailability (AUC and Cmax) of CLARINEX Oral Solution.

The pharmacokinetic profile of CLARINEX RediTabs Tablets was evaluated in a three-way crossover study in 24 adult volunteers. A single CLARINEX RediTabs Tablet containing 5 mg of desloratadine was bioequivalent to a single 5-mg CLARINEX RediTabs Tablet (original formulation) for both desloratadine and 3-hydroxydesloratadine. Food and water had no effect on the bioavailability (AUC and Cmax) of CLARINEX RediTabs Tablets.

Distribution

Desloratadine and 3-hydroxydesloratadine are approximately 82% to 87% and 85% to 89% bound to plasma proteins, respectively. Protein binding of desloratadine and 3-hydroxydesloratadine was unaltered in subjects with impaired renal function.

Metabolism

Desloratadine (a major metabolite of loratadine) is extensively metabolized to 3-hydroxydesloratadine, an active metabolite, which is subsequently glucuronidated. The enzyme(s) responsible for the formation of 3-hydroxydesloratadine have not been identified. Data from clinical trials indicate that a subset of the general population has a decreased ability to form 3-hydroxydesloratadine, and are poor metabolizers of desloratadine. In pharmacokinetic studies (n=3748), approximately 6% of subjects were poor metabolizers of desloratadine (defined as a subject with an AUC ratio of 3-hydroxydesloratadine to desloratadine less than 0.1, or a subject with a desloratadine half-life exceeding 50 hours). These pharmacokinetic studies included subjects between the ages of 2 and 70 years, including 977 subjects aged 2 to 5 years, 1575 subjects aged 6 to 11 years, and 1196 subjects aged 12 to 70 years. There was no difference in the prevalence of poor metabolizers across age groups. The frequency of poor metabolizers was higher in Blacks (17%, n=988) as compared to Caucasians (2%, n=1,462) and Hispanics (2%, n=1,063). The median exposure (AUC) to desloratadine in the poor metabolizers was approximately 6-fold greater than in the subjects who are not poor metabolizers. Subjects who are poor metabolizers of desloratadine cannot be prospectively identified and will be exposed to higher levels of desloratadine following dosing with the recommended dose of desloratadine. In multidose clinical safety studies, where metabolizer status was identified, a total of 94 poor metabolizers and 123 normal metabolizers were enrolled and treated with CLARINEX Oral Solution for 15–35 days. In these studies, no overall differences in safety were observed between poor metabolizers and normal metabolizers. Although not seen in these studies, an increased risk of exposure-related adverse events in patients who are poor metabolizers cannot be ruled out.

Elimination

The mean plasma elimination half-life of desloratadine was approximately 27 hours. Cmax and AUC values increased in a dose proportional manner following single oral doses between 5 and 20 mg. The degree of accumulation after 14 days of dosing was consistent with the half-life and dosing frequency. A human mass balance study documented a recovery of approximately 87% of the ^14C-desloratadine dose, which was equally distributed in urine and feces as metabolic products. Analysis of plasma 3-hydroxydesloratadine showed similar Tmax and half-life values compared to desloratadine.

Special Populations

Geriatric Subjects: In older subjects (≥65 years old; n=17) following multiple-dose administration of CLARINEX Tablets, the mean Cmax and AUC values for desloratadine were 20% greater than in younger subjects (<65 years old). The oral total body clearance (CL/F) when normalized for body weight was similar between the two age groups. The mean plasma elimination half-life of desloratadine was 33.7 hr in subjects ≥65 years old. The pharmacokinetics for 3-hydroxydesloratadine appeared unchanged in older versus younger subjects. These age-related differences are unlikely to be clinically relevant and no dosage adjustment is recommended in elderly subjects.

Pediatric Subjects: In subjects 6 to 11 years old, a single dose of 5 mL of CLARINEX Oral Solution containing 2.5 mg of desloratadine, resulted in desloratadine plasma concentrations similar to those achieved in adults administered a single 5-mg CLARINEX Tablet. In subjects 2 to 5 years old, a single dose of 2.5 mL of CLARINEX Oral Solution containing 1.25 mg of desloratadine, resulted in desloratadine plasma concentrations similar to those achieved in adults administered a single 5-mg CLARINEX Tablet. However, the Cmax and AUC of the metabolite (3-hydroxydesloratadine) were 1.27 and 1.61 times higher for the 5-mg dose of Oral Solution administered in adults compared to the Cmax and AUC obtained in children 2 to 11 years of age receiving 1.25–2.5 mg of CLARINEX Oral Solution.

A single dose of either 2.5 mL or 1.25 mL of CLARINEX Oral Solution containing 1.25 mg or 0.625 mg, respectively, of desloratadine was administered to subjects 6 to 11 months of age and 12 to 23 months of age. The results of a population pharmacokinetic analysis indicated that a dose of 1 mg for subjects aged 6 to 11 months and 1.25 mg for subjects 12 to 23 months of age is required to obtain desloratadine plasma concentrations similar to those achieved in adults administered a single 5-mg dose of CLARINEX Oral Solution.

The CLARINEX RediTabs 2.5-mg tablet has not been evaluated in pediatric patients. Bioequivalence of the CLARINEX RediTabs Tablet and the original CLARINEX RediTabs Tablets was established in adults. In conjunction with the dose-finding studies in pediatrics described, the pharmacokinetic data for CLARINEX RediTabs Tablets supports the use of the 2.5-mg dose strength in pediatric patients 6 to 11 years of age.

Renally Impaired: Desloratadine pharmacokinetics following a single dose of 7.5 mg were characterized in patients with mild (n=7; creatinine clearance 51–69 mL/min/1.73 m^2), moderate (n=6; creatinine clearance 34–43 mL/min/1.73 m^2), and severe (n=6; creatinine clearance 5–29 mL/min/1.73 m^2) renal impairment or hemodialysis dependent (n=6) patients. In patients with mild and moderate renal impairment, median Cmax and AUC values increased by approximately 1.2- and 1.9-fold, respectively, relative to subjects with normal renal function. In patients with severe renal impairment or who were hemodialysis dependent, Cmax and AUC values increased by approximately 1.7- and 2.5-fold, respectively. Minimal changes in 3-hydroxydesloratadine concentrations were observed. Desloratadine and 3-hydroxydesloratadine were poorly removed by hemodialysis. Plasma protein binding of desloratadine and 3-hydroxydesloratadine was unaltered by renal impairment. Dosage adjustment for patients with renal impairment is recommended [see Dosage and Administration (2.5)].

Hepatically Impaired: Desloratadine pharmacokinetics were characterized following a single oral dose in patients with mild (n=4), moderate (n=4), and severe (n=4) hepatic impairment as defined by the Child-Pugh classification of hepatic function and 8 subjects with normal hepatic function. Patients with hepatic impairment, regardless of severity, had approximately a 2.4-fold increase in AUC as compared with normal subjects. The apparent oral clearance of desloratadine in patients with mild, moderate, and severe hepatic impairment was 37%, 36%, and 28% of that in normal subjects, respectively. An increase in the mean elimination half-life of desloratadine in patients with hepatic impairment was observed. For 3-hydroxydesloratadine, the mean Cmax and AUC values for patients with hepatic impairment were not statistically significantly different from subjects with normal hepatic function. Dosage adjustment for patients with hepatic impairment is recommended [see Dosage and Administration (2.5)].

Gender: Female subjects treated for 14 days with CLARINEX Tablets had 10% and 3% higher desloratadine Cmax and AUC values, respectively, compared with male subjects. The 3-hydroxydesloratadine Cmax and AUC values were also increased by 45% and 48%, respectively, in females compared with males. However, these apparent differences are not likely to be clinically relevant and therefore no dosage adjustment is recommended.

Race: Following 14 days of treatment with CLARINEX Tablets, the Cmax and AUC values for desloratadine were 18% and 32% higher, respectively, in Blacks compared with Caucasians. For 3-hydroxydesloratadine there was a corresponding 10% reduction in Cmax and AUC values in Blacks compared to Caucasians. These differences are not likely to be clinically relevant and therefore no dose adjustment is recommended.

Drug Interactions: In two controlled crossover clinical pharmacology studies in healthy male (n=12 in each study) and female (n=12 in each study) volunteers, desloratadine 7.5 mg (1.5 times the daily dose) once daily was coadministered with erythromycin 500 mg every 8 hours or ketoconazole 200 mg every 12 hours for 10 days. In three separate controlled, parallel group clinical pharmacology studies, desloratadine at the clinical dose of 5 mg has been coadministered with azithromycin 500 mg followed by 250 mg once daily for 4 days (n=18) or with fluoxetine 20 mg once daily for 7 days after a 23-day pretreatment period with fluoxetine (n=18) or with cimetidine 600 mg every 12 hours for 14 days (n=18) under steady-state conditions to normal healthy male and female volunteers. Although increased plasma concentrations (Cmax and AUC0-24 hrs) of desloratadine and 3-hydroxydesloratadine were observed (see Table 2), there were no clinically relevant changes in the safety profile of desloratadine, as assessed by electrocardiographic parameters (including the corrected QT interval), clinical laboratory tests, vital signs, and adverse events.

Table 2: Changes in Desloratadine and 3-Hydroxydesloratadine Pharmacokinetics in Healthy Male and Female Volunteers
 | Desloratadine |  | 3-Hydroxydesloratadine
 | Cmax | AUC0-24 hrs | Cmax | AUC0-24 hrs
Erythromycin (500 mg Q8h) | + 24% | + 14% | + 43% | + 40%
Ketoconazole (200 mg Q12h) | + 45% | + 39% | + 43% | + 72%
Azithromycin (500 mg day 1, 250 mg QD x 4 days) | + 15% | + 5% | + 15% | + 4%
Fluoxetine (20 mg QD) | + 15% | + 0% | + 17% | + 13%
Cimetidine (600 mg Q12h) | + 12% | + 19% | - 11% | - 3%

13 NONCLINICAL TOXICOLOGY

13.1 Carcinogenesis, Mutagenesis, Impairment of Fertility

Carcinogenicity Studies

The carcinogenic potential of desloratadine was assessed using a loratadine study in rats and a desloratadine study in mice. In a 2-year study in rats, loratadine was administered in the diet at doses up to 25 mg/kg/day (approximately 45 times the summed AUC-based exposure of desloratadine and its metabolite at the RHD). A significantly higher incidence of hepatocellular tumors (combined adenomas and carcinomas) was observed in males given 10 mg/kg/day of loratadine (approximately 10 times the summed AUC-based exposure of desloratadine and its metabolite at the RHD) and in males and females given 25 mg/kg/day of loratadine. The clinical significance of these findings during long-term use of desloratadine is not known. In a 2-year dietary study in mice, males and females given up to 16 mg/kg/day and 32 mg/kg/day desloratadine, respectively (approximately 30 and 70 times the summed AUC-based exposure of desloratadine and its metabolite at the RHD, respectively), did not show significant increases in the incidence of any tumors.

Genotoxicity Studies

In genotoxicity studies with desloratadine, there was no evidence of genotoxic potential in a reverse mutation assay (Salmonella/E. coli mammalian microsome bacterial mutagenicity assay) or in 2 assays for chromosomal aberrations (human peripheral blood lymphocyte clastogenicity assay and mouse bone marrow micronucleus assay).

Impairment of Fertility

In a female fertility study, desloratadine was given to female rats orally 14 days prior to and throughout mating until Gestation Day 7 at doses of 6, 12 and 24 mg/kg/day. An increase in preimplantation loss and a decrease in number of implantations and fetuses noted at 24 mg/kg (approximately 200 times the summed AUC-based exposure of desloratadine and its metabolite at the RHD) was likely due to maternal toxicities including reduced body weight gain and food consumption. In a male fertility study in rats, desloratadine was given orally to male rats for 70 days prior to mating and throughout the mating period (total dosing period 106-108 days) at doses of 3, 12 and 40 mg/kg/day. Reduced body weight gain, food consumption, and absolute organ weights of testes, epididymis, and cauda epididymis were noted at 40 mg/kg/day. A male-specific decrease in fertility, demonstrated by reduced female conception rates, decreased sperm numbers and motility, and histopathologic changes in testes and epididymis, occurred at a dose of 12 mg/kg or greater (approximately 65 times or greater than the summed AUC-based exposure of desloratadine and its metabolite at the RHD). Desloratadine had no effect on male fertility in rats at 3 mg/kg/day (approximately 10 times the summed AUC-based exposure of desloratadine and its metabolite at the RHD).

14 CLINICAL STUDIES

14.1 Seasonal Allergic Rhinitis

The clinical efficacy and safety of CLARINEX Tablets were evaluated in over 2300 patients 12 to 75 years of age with seasonal allergic rhinitis. A total of 1838 patients received 2.5 to 20 mg/day of CLARINEX in 4 double-blind, randomized, placebo-controlled clinical trials of 2 to 4 weeks' duration conducted in the United States. The results of these studies demonstrated the efficacy and safety of CLARINEX 5 mg in the treatment of adult and adolescent patients with seasonal allergic rhinitis. In a dose-ranging trial, CLARINEX 2.5 to 20 mg/day was studied. Doses of 5, 7.5, 10, and 20 mg/day were superior to placebo; and no additional benefit was seen at doses above 5.0 mg. In the same study, an increase in the incidence of somnolence was observed at doses of 10 mg/day and 20 mg/day (5.2% and 7.6%, respectively), compared to placebo (2.3%).

In two 4-week studies of 924 patients (aged 15 to 75 years) with seasonal allergic rhinitis and concomitant asthma, CLARINEX Tablets 5 mg once daily improved rhinitis symptoms, with no decrease in pulmonary function. This supports the safety of administering CLARINEX Tablets to adult patients with seasonal allergic rhinitis with mild to moderate asthma.

CLARINEX Tablets 5 mg once daily significantly reduced the Total Symptom Score (the sum of individual scores of nasal and non-nasal symptoms) in patients with seasonal allergic rhinitis. See Table 3.

Table 3: TOTAL SYMPTOM SCORE (TSS) Changes in a 2-Week Clinical Trial in Patients with Seasonal Allergic Rhinitis
Treatment Group (n) | Mean Baseline [At baseline, a total nasal symptom score (sum of 4 individual symptoms) of at least 6 and a total non-nasal symptom score (sum of 4 individual symptoms) of at least 5 (each symptom scored 0 to 3 where 0=no symptom and 3=severe symptoms) was required for trial eligibility. TSS ranges from 0=no symptoms to 24=maximal symptoms.] (SEM) | Change from Baseline [Mean reduction in TSS averaged over the 2-week treatment period.] (SEM) | Placebo Comparison (P-value)
CLARINEX 5.0 mg (171) | 14.2 (0.3) | -4.3 (0.3) | P<0.01
Placebo (173) | 13.7 (0.3) | -2.5 (0.3)
SEM=Standard Error of the Mean

There were no significant differences in the effectiveness of CLARINEX Tablets 5 mg across subgroups of patients defined by gender, age, or race.

14.2 Perennial Allergic Rhinitis

The clinical efficacy and safety of CLARINEX Tablets 5 mg were evaluated in over 1300 patients 12 to 80 years of age with perennial allergic rhinitis. A total of 685 patients received 5 mg/day of CLARINEX in two double-blind, randomized, placebo-controlled clinical trials of 4 weeks' duration conducted in the United States and internationally. In one of these studies CLARINEX Tablets 5 mg once daily was shown to significantly reduce the Total Symptom Score in patients with perennial allergic rhinitis (Table 4).

Table 4: TOTAL SYMPTOM SCORE (TSS) Changes in a 4-Week Clinical Trial in Patients with Perennial Allergic Rhinitis
Treatment Group (n) | Mean Baseline [At baseline, average of total symptom score (sum of 5 individual nasal symptoms and 3 non-nasal symptoms, each symptom scored 0 to 3 where 0=no symptom and 3=severe symptoms) of at least 10 was required for trial eligibility. TSS ranges from 0=no symptoms to 24=maximal symptoms.] (SEM) | Change from Baseline [Mean reduction in TSS averaged over the 4-week treatment period.] (SEM) | Placebo Comparison (P-value)
CLARINEX 5.0 mg (337) | 12.37 (0.18) | -4.06 (0.21) | P=0.01
Placebo (337) | 12.30 (0.18) | -3.27 (0.21)
SEM=Standard Error of the Mean

14.3 Chronic Idiopathic Urticaria

The efficacy and safety of CLARINEX Tablets 5 mg once daily was studied in 416 chronic idiopathic urticaria patients 12 to 84 years of age, of whom 211 received CLARINEX. In two double-blind, placebo-controlled, randomized clinical trials of six weeks duration, at the pre-specified one-week primary time point evaluation, CLARINEX Tablets significantly reduced the severity of pruritus when compared to placebo (Table 5). Secondary endpoints were also evaluated, and during the first week of therapy CLARINEX Tablets 5 mg reduced the secondary endpoints, "Number of Hives" and the "Size of the Largest Hive," when compared to placebo.

Table 5: PRURITUS SYMPTOM SCORE Changes in the First Week of a Clinical Trial in Patients with Chronic Idiopathic Urticaria
Treatment Group (n) | Mean Baseline (SEM) | Change from Baseline [Mean reduction in pruritus averaged over the first week of treatment.] (SEM) | Placebo Comparison (P-value)
CLARINEX 5.0 mg (115) | 2.19 (0.04) | -1.05 (0.07) | P<0.01
Placebo (110) | 2.21 (0.04) | -0.52 (0.07)
Pruritus scored 0 to 3 where 0=no symptom to 3=maximal symptom
SEM=Standard Error of the Mean

The clinical safety of CLARINEX Oral Solution was documented in three, 15-day, double-blind, placebo-controlled safety studies in pediatric subjects with a documented history of allergic rhinitis, chronic idiopathic urticaria, or subjects who were candidates for antihistamine therapy. In the first study, 2.5 mg of CLARINEX Oral Solution was administered to 60 pediatric subjects 6 to 11 years of age. The second study evaluated 1.25 mg of CLARINEX Oral Solution administered to 55 pediatric subjects 2 to 5 years of age. In the third study, 1.25 mg of CLARINEX Oral Solution was administered to 65 pediatric subjects 12 to 23 months of age and 1.0 mg of CLARINEX Oral Solution was administered to 66 pediatric subjects 6 to 11 months of age. The results of these studies demonstrated the safety of CLARINEX Oral Solution in pediatric subjects 6 months to 11 years of age.

16 HOW SUPPLIED/STORAGE AND HANDLING

CLARINEX Tablets:

- Embossed “C5”, light blue, film-coated tablets that are packaged in high-density polyethylene plastic bottles of 100 (NDC 78206-119-01).
- Embossed with elongated letters “S” and “P”, light blue, film-coated tablets that are packaged in high-density polyethylene plastic bottles of 100 (NDC 78206-188-01).

Storage

- CLARINEX Tablets: Protect Unit-of-Use packaging and Unit-Dose Hospital Pack from excessive moisture. Store at 25°C (77°F); excursions permitted to 15°C to 30°C (59°F to 86°F) [see USP Controlled Room Temperature]. Heat Sensitive. Avoid exposure at or above 30°C (86°F).

17 PATIENT COUNSELING INFORMATION

Advise the patient to read the FDA-approved patient labeling (Patient Information).

17.1 Information for Patients

- Patients should be instructed to use CLARINEX as directed.
- As there are no food effects on bioavailability, patients can be instructed that CLARINEX Tablets, Oral Solution, or RediTabs Tablets may be taken without regard to meals.
- Patients should be advised not to increase the dose or dosing frequency as studies have not demonstrated increased effectiveness at higher doses and somnolence may occur.
- Phenylketonurics: CLARINEX RediTabs Tablets contain phenylalanine.

Manufactured for: Organon LLC, a subsidiary of
ORGANON & Co.,
Jersey City, NJ 07302, USA

For patent information: www.organon.com/our-solutions/patent/

© 2022 Organon group of companies. All rights reserved.

uspi-og4117-mf-2208r001

PATIENT INFORMATION

CLARINEX® (CLA-RI-NEX) (desloratadine) Tablets, RediTabs®, and Oral Solution

Read the Patient Information that comes with CLARINEX® before you start taking it and each time you get a refill. There may be new information. This leaflet is a summary of the information for patients. Your doctor or pharmacist can give you additional information. This leaflet does not take the place of talking to your doctor about your medical condition or treatment.

What is CLARINEX?

CLARINEX is a prescription medicine that contains the medicine desloratadine (an antihistamine).

CLARINEX is used to help control the symptoms of:

- seasonal allergic rhinitis (sneezing, stuffy nose, runny nose and itching of the nose) in people 2 years of age and older.
- perennial allergic rhinitis (sneezing, stuffy nose, runny nose and itching of the nose) in people 6 months of age and older.
- chronic idiopathic urticaria (long-term itching) and to reduce the number and size of hives in people 6 months of age and older.

CLARINEX is not for children younger than 6 months of age.

Who should not take CLARINEX?

Do not take CLARINEX if you:

- are allergic to desloratadine or any of the ingredients in CLARINEX Tablets, CLARINEX RediTabs® or CLARINEX Oral Solution. See the end of this leaflet for a complete list of ingredients for the CLARINEX Tablets.
- are allergic to loratadine (Alavert, Claritin).

Talk to your doctor before taking this medicine if you have any questions about whether or not to take this medicine.

What should I tell my doctor before taking CLARINEX?

Before you take CLARINEX, tell your doctor if you:

- have liver or kidney problems.
- have any other medical conditions.
- are pregnant or plan to become pregnant. It is not known if CLARINEX will harm your unborn baby. Talk to your doctor if you are pregnant or plan to become pregnant.
- are breast-feeding or plan to breast-feed. CLARINEX can pass into your breast milk. Talk to your doctor about the best way to feed your baby if you take CLARINEX.

Tell your doctor about all the medicines you take, including prescription and non-prescription medicines, vitamins and herbal supplements. CLARINEX may affect the way other medicines work, and other medicines may affect how CLARINEX works. Especially tell your doctor if you take:

- ketoconazole (Nizoral)
- erythromycin (Ery-tab, Eryc, PCE)
- azithromycin (Zithromax, Zmax)
- antihistamines
- fluoxetine (Prozac)
- cimetidine (Tagamet)

Know the medicines you take. Keep a list of your medicines and show it to your doctor and pharmacist when you get a new medicine.

How should I take CLARINEX?

- Take CLARINEX exactly as your doctor tells you to take it.
- Do not change your dose of CLARINEX or take more often than prescribed.
- CLARINEX can be taken with or without food.
- Place CLARINEX RediTabs Tablet on your tongue and allow it to dissolve before swallowing. CLARINEX RediTabs can be taken with or without water. Take your CLARINEX RediTabs Tablet right away after opening the blister.
- Take CLARINEX Oral Solution with a measuring dropper or oral syringe that can measure 2 mL or 2.5 mL. Ask your pharmacist for a dropper or syringe if you do not have one.
- If you take too much CLARINEX, call your doctor or get medical attention right away.

What are the possible side effects of CLARINEX Tablets?

CLARINEX may cause serious side effects, including:

- Allergic reactions. Stop taking CLARINEX and call your doctor right away or get emergency help if you have any of these symptoms:
  - rash
  - itching
  - hives
  - swelling of your lips, tongue, face, and throat
  - shortness of breath or trouble breathing

The most common side effects of CLARINEX in adults and children 12 years of age and older with allergic rhinitis include:

- sore throat
- dry mouth
- muscle pain
- tiredness
- sleepiness
- menstrual pain

Increased sleepiness or tiredness can happen if you take more CLARINEX than your doctor prescribed to you.

Tell your doctor if you have any side effect that bothers you or that does not go away.

These are not all of the possible side effects of CLARINEX. For more information, ask your doctor or pharmacist.

Call your doctor for medical advice about side effects. You may report side effects to FDA at 1-800-FDA-1088.

How should I store CLARINEX?

- Store CLARINEX Tablets between 59°F to 86°F (15°C to 30°C).
- CLARINEX Tablets are sensitive to heat. Do not store above 86°F (30°C).
- Protect CLARINEX Tablets from moisture.

Keep CLARINEX Tablets, RediTabs Tablets, and Oral Solution and all medicines out of the reach of children.

General information about CLARINEX

Medicines are sometimes prescribed for purposes other than those listed in a patient information leaflet. Do not use CLARINEX for a condition for which it was not prescribed. Do not give CLARINEX to other people, even if they have the same condition you have. It may harm them.

This Patient Information leaflet summarizes the most important information about CLARINEX. If you would like more information, talk with your doctor. You can ask your pharmacist or doctor for information about CLARINEX that is written for health professionals.

What are the ingredients in CLARINEX?

Active ingredient: desloratadine

Patients with Phenylketonuria: CLARINEX RediTabs Tablets contain phenylalanine.

Inactive ingredients in CLARINEX Tablets: dibasic calcium phosphate dihydrate USP, microcrystalline cellulose NF, corn starch NF, talc USP, carnauba wax NF, white wax NF, coating material consisting of lactose monohydrate, hypromellose, titanium dioxide, polyethylene glycol, and FD&C Blue #2 Aluminum Lake.

CLARINEX Tablets are
Manufactured for: Organon LLC, a subsidiary of
ORGANON & Co.,
Jersey City, NJ 07302, USA

For patent information: www.organon.com/our-solutions/patent/

The trademarks depicted herein are owned by their respective companies.

Copyright © 2021 Organon Global Inc.
All rights reserved.

Revised: 6/2021

usppi-og4117-mtl-2106r000

PRINCIPAL DISPLAY PANEL - 100 Tablet Bottle Label

NDC 78206-119-01
100 Tablets

CLARINEX®
(desloratadine)
5 mg TABLETS

Rx only

actual size ®

PRINCIPAL DISPLAY PANEL - 100 Tablet Bottle Label

NDC 78206-188-01
100 Tablets

CLARINEX®
(desloratadine)
5 mg TABLETS

Rx only

actual size ®